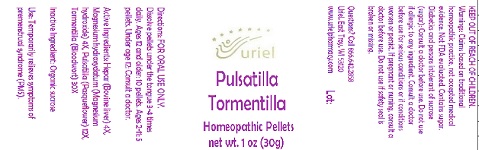 DRUG LABEL: Pulsatilla Tormentilla
NDC: 48951-8360 | Form: PELLET
Manufacturer: Uriel Pharmacy Inc.
Category: homeopathic | Type: HUMAN OTC DRUG LABEL
Date: 20191101

ACTIVE INGREDIENTS: PULSATILLA VULGARIS 12 [hp_X]/1 1; POTENTILLA ERECTA ROOT 30 [hp_X]/1 1; BEEF LIVER 4 [hp_X]/1 1; HYDROXIDE ION 4 [hp_X]/1 1
INACTIVE INGREDIENTS: SUCROSE

Pulsatilla Tormentilla

INDICATIONS AND USAGE

Directions: FOR ORAL USE ONLY.

DOSAGE AND ADMINISTRATION

Dissolve pellets under the tongue 3-4 times daily. Ages 12 and older: 10 pellets. Ages 2-11: 5 pellets. Under age 12: Consult a doctor.

ACTIVE INGREDIENT

Active Ingredients: Hepar (Bovine liver) 4X, Magnesium hydroxydatum (Magnesium hydroxide) 4X, Pulsatilla (Pasqueflower) 12X, Tormentilla (Bloodwort) 30X

Inactive Ingredient: Organic sucrose

PURPOSE

Use: Temporarily relieves symptoms of premenstrual syndrome (PMS).

KEEP OUT OF REACH OF CHILDREN.

WARNINGS

Warnings: Claims based on traditional homeopathic practice, not accepted medical evidence. Not FDA evaluated. Contains sugar. Diabetics and persons intolerant of sucrose (sugar): Consult a doctor before use. Do not use if allergic to any ingredient. Consult a doctor before use for serious conditions or if conditions worsen or persist. If pregnant or nursing, consult a doctor before use. Do not use if safety seal is broken or missing.

Questions? Call 866.642.2858
Uriel, East Troy, WI 53120
www.urielpharmacy.com